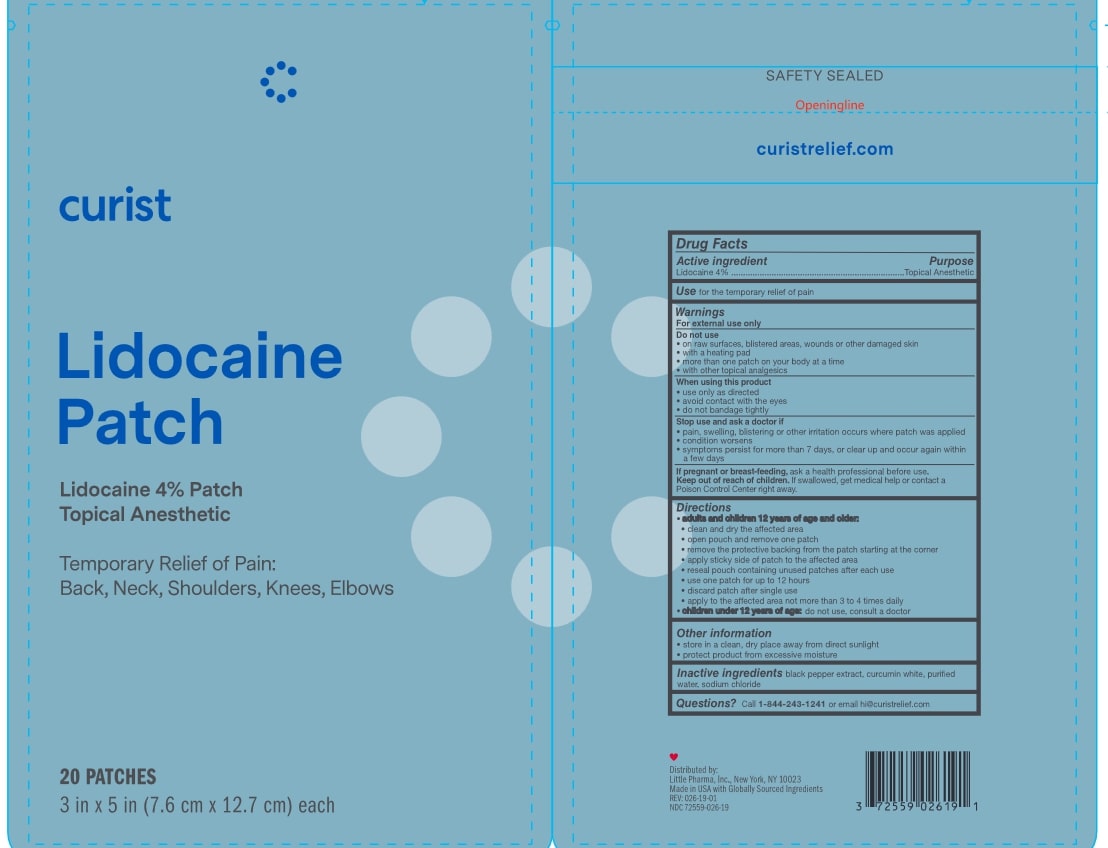 DRUG LABEL: Curist Lidocaine Patch
NDC: 72559-026 | Form: PATCH
Manufacturer: Little Pharma, Inc.
Category: otc | Type: HUMAN OTC DRUG LABEL
Date: 20240612

ACTIVE INGREDIENTS: LIDOCAINE 4 g/100 g
INACTIVE INGREDIENTS: WATER; BLACK PEPPER; CURCUMINOIDS; SODIUM CHLORIDE

Drug Facts

Active ingredient

Lidocaine 4%

Purpose

Topical Anesthetic

Use

for the temporary relief of pain

Warnings

For external use only

Do not use

- on raw surfaces, blistered areas, wounds or other damaged skin
- with a heating pad
- more than one patch on your body at a time
- with other topical analgesics

When using this product

- use only as directed
- avoid contact with the eyes
- do not bandage tightly

Stop use and ask a doctor if

- pain, swelling, blistering or other irritation occurs where patch was applied
- condition worsens
- symptoms persist for more than 7 days, or clear up and occur again within a few days

PREGNANCY OR BREAST FEEDING

If pregnant or breast-feeding, ask a health professional before use.

Keep out of reach of children. If swallowed, get medical help or contact a Poison Control Center right away.

Directions

- adults and children 12 years of age and older:
- clean and dry the affected area
- open pouch and remove one patch
- remove the protective backing from the patch starting at the corner
- apply sticky side of patch to the affected area
- reseal pouch containing unused patches after each use
- use one patch for up to 12 hours
- discard patch after single use
- apply to the affected area not more than 3 to 4 times daily
- children under 12 years of age: do not use, consult a doctor

Other information

- store in a clean, dry place away from direct sunlight
- protect product from excessive moisture

Inactive ingredients

black pepper extract, curcumin white, purified water, sodium chloride

Questions?

Call 1-844-243-1241 or email hi@curistrelief.com

SAFETY SEALED

curistrelief.com

Distributed by:

Little Pharma, Inc., New York, NY 10023

Made in USA with Globally Sourced Ingredients

REV: 026-19-01

NDC: 72559-026-19

PACKAGE LABEL

curist

Lidocaine Patch

Lidocaine 4% Patch

Topical Anesthetic

Temporary Relief of Pain:

Back, Neck, Shoulders, Knees, Elbows

20 Patches

3 in x 5 in (7.6 cm x 12.7 cm) each